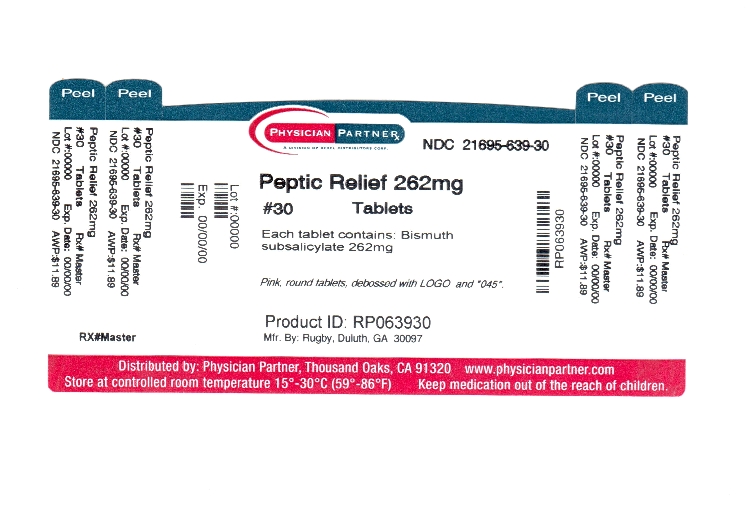 DRUG LABEL: Peptic Relief
NDC: 21695-639 | Form: TABLET
Manufacturer: Rebel Distributors Corp
Category: otc | Type: HUMAN OTC DRUG LABEL
Date: 20111230

ACTIVE INGREDIENTS: BISMUTH SUBSALICYLATE 262 mg/1 1
INACTIVE INGREDIENTS: D&C RED NO. 27; CALCIUM CARBONATE; DEXTROSE; MAGNESIUM STEARATE; MALTODEXTRIN; SILICON DIOXIDE; SORBITOL

Peptic Relief Drug Facts

Active ingredient

Bismuth Subsalicytate 262mg

Purpose

Anti-diarrheal/Upset stomach reliever

Keep Out of Reach of Children

In case of overdose,, get medical help or contact a Poison Control Center right away.

Uses

* Controls diarrhea

* Relieves upset stomach due to overindulgence in food or drink

Warnings

Reye's syndrome: Children and teenagers who have or are recovering from chicken pox or flu-like symptoms should not use this product. When using this product, if changes in behavior with nausea and vomiting occur, consult a doctor because these symptoms could be an early sign of Reye's syndrome, a rare but serious illness.

Allergy Alert: Do not take if you are

* allergic to salicylates (including aspirin)

* taking other salicylate products

Do not use

* if you have bloody or black stool

* if you have an ulcer or bleeding problem

Ask a doctor before use if you have

* fever

* mucus in the stool

Drug Facts

Ask a doctor or pharmacist before use if you are taking any drug for

* anticoagulation (thinning the blood)

* diabetes

* gout

* arthritis

When using this product a temporary, but harmless, darkening of the stool and/or tongue may occur.

Stop use and ask a doctor if

* symptoms get worse

* ringing in the ears or loss of hearing occurs

* diarrhea lasts more than 2 days

If pregnant or breast-feeding, ask a health professional before use.

Directions

* drink plenty of clear fluids to help prevent dehydration caused by diarrhea

* repeat dosage every 1/2 to 1 hour as needed

* do not take more than 8 doses in 24 hours

* use until diarrhea stops but not more than 2 days

* adults and children 12 years and over:

2 tablets

* children under 12 years: ask a doctor

Other information

* each tablet contains: calcium 77mg

salicylate 102mg

* store at 15°-30°C (59°-86°F)

* protect from moisture

Inactive ingredients

D&C red #27 (al-lake), dextrose, flavor (cherry), magnesium stearate, maltodextrin, silicon dioxide, sorbitol

Questions or comments?

call 1-800-645-2158, 9 am-5 pm EST, Monday-Friday.